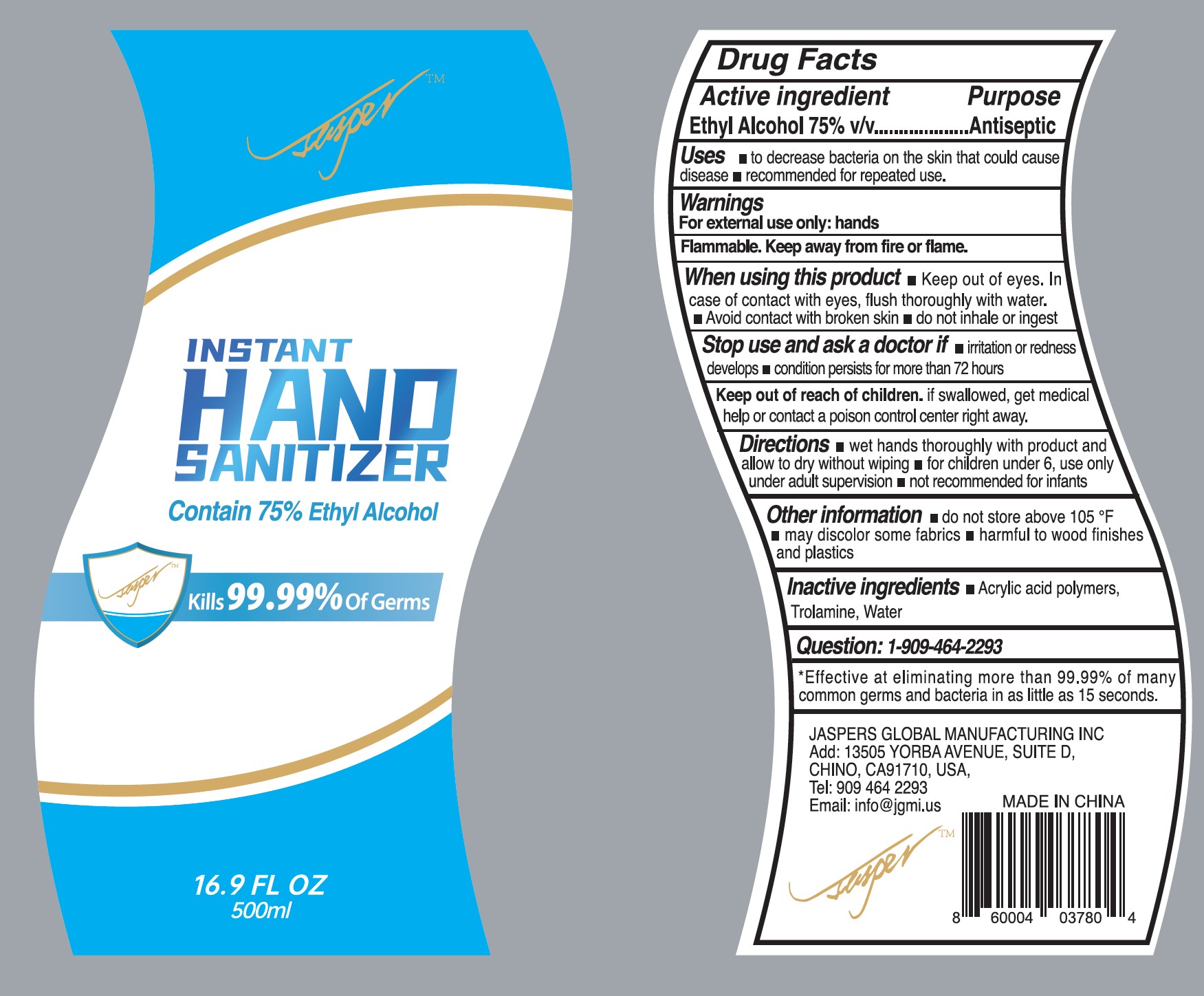 DRUG LABEL: 75% alcohol hand sanitizer
NDC: 75617-002 | Form: GEL
Manufacturer: JASPERS GLOBAL MANUFACTURING INC
Category: otc | Type: HUMAN OTC DRUG LABEL
Date: 20230213

ACTIVE INGREDIENTS: ALCOHOL 75 mL/100 mL
INACTIVE INGREDIENTS: CARBOMER 940; WATER; TROLAMINE

75% alcohol hand sanitizer

Active ingredient

Alcohol 75% v/v. Purpose: Antiseptic

Purpose

Antiseptic. Hand senitizer

Uses

- to decrease bacteria on the skin that could cause disease
- recommended for repeated use

Warnings

For external use only: hands

Flammable. Keep away from fire or flame.

When using this product

- Keep out of eyes. In case of contact with eyes, flush thoroughly with water.
- Avoid contact with broken skin.
- Do not inhale or ingest

Stop use and ask a doctor if

- irritation or redness develops
- condition persists for more than 72 hours

KEEP OUT OF REACH OF CHILDREN

Keep it out of reach of children. If swallowed, get medical help or contact a poison control center right away.

Directions

- wet hands thoroughly with product and allow to dry without wiping.
- for children under 6, use only under adult supervision
- not recommended for infants

Other information

- do not store above 105F
- may discolor some fabrics
- harmful to wood finishes and plastics

Inactive ingredients

Acrylic acid polymer, triethanolamine, water

Package Label - Principal Display Panel

500mL NDC: 75617-002-01